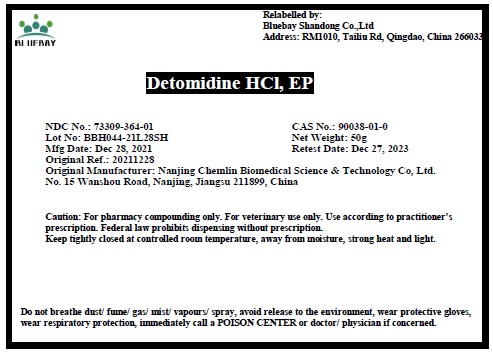 DRUG LABEL: Detomidine HCl
NDC: 73309-364 | Form: POWDER
Manufacturer: BLUEBAY SHANDONG CO.,LTD
Category: other | Type: BULK INGREDIENT - ANIMAL DRUG
Date: 20220311

ACTIVE INGREDIENTS: DETOMIDINE HYDROCHLORIDE 1 g/1 g

Detomidine HCl